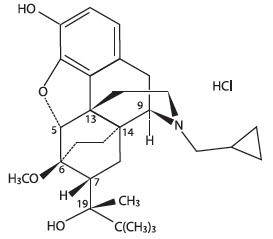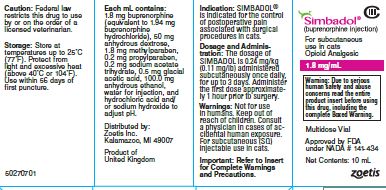 DRUG LABEL: Simbadol
NDC: 54771-4131 | Form: INJECTION
Manufacturer: Zoetis Inc.
Category: animal | Type: PRESCRIPTION ANIMAL DRUG LABEL
Date: 20230306
DEA Schedule: CIII

ACTIVE INGREDIENTS: BUPRENORPHINE HYDROCHLORIDE 1.8 mg/1 mL
INACTIVE INGREDIENTS: ANHYDROUS DEXTROSE 50 mg/1 mL; METHYLPARABEN 1.8 mg/1 mL; PROPYLPARABEN 0.2 mg/1 mL; SODIUM ACETATE 0.2 mg/1 mL; ACETIC ACID 0.5 mg/1 mL; ALCOHOL 100.0 mg/1 mL; WATER; HYDROCHLORIC ACID; SODIUM HYDROXIDE

Simbadol®

For Use in Cats Only

Simbadol®

(buprenorphine injection)

1.8 mg/mL

For subcutaneous use in cats

Opioid Analgesic

CAUTION

Federal law restricts this drug to use by or on the order of a licensed veterinarian.

HUMAN SAFETY WARNING

Abuse Potential

SIMBADOL contains buprenorphine (1.8 mg/mL), an opioid agonist and Schedule III controlled substance with an abuse potential similar to other Schedule III opioids. Buprenorphine has certain opioid properties that in humans may lead to dependence of the morphine type. Abuse of buprenorphine may lead to physical dependence or psychological dependence. The risk of abuse by humans should be considered when storing, administering, and disposing of SIMBADOL. Persons at increased risk for opioid abuse include those with a personal or family history of substance abuse (including drug or alcohol abuse or addiction) or mental illness (suicidal depression).

Life-Threatening Respiratory Depression

Respiratory depression, including fatal cases, may occur with abuse of SIMBADOL.

Additive CNS Depressant Effects

SIMBADOL has additive CNS depressant effects when used with alcohol, other opioids, or illicit drugs that cause central nervous system depression.

Accidental Exposure

Because of the potential for adverse reactions associated with accidental injection, SIMBADOL should only be administered by veterinarians or veterinary technicians who are trained in the handling of potent opioids.

See Human Safety for detailed information.

DESCRIPTION

SIMBADOL is a clear, colorless to slightly yellow, sterile, injectable solution intended for subcutaneous administration for use in cats. Each milliliter of SIMBADOL contains 1.8 mg buprenorphine (equivalent to 1.94 mg buprenorphine hydrochloride), 50 mg anhydrous dextrose, 1.8 mg methylparaben, 0.2 mg propylparaben, 0.2 mg sodium acetate trihydrate, 0.5 mg glacial acetic acid, 100.0 mg anhydrous ethanol, water for injection, and hydrochloric acid and/or sodium hydroxide to adjust pH. Buprenorphine belongs to the opioid class of drugs and is a narcotic under the Controlled Substances Act due to its chemical derivation from thebaine. Buprenorphine hydrochloride is a weakly acidic, white or off-white crystalline powder with limited solubility in water. Chemically, it is 17-(cyclopropylmethyl)- α-(1,1-dimethylethyl)-4, 5-epoxy-18,19-dihydro-3-hydroxy-6-methoxy-α-methyl-6, 14-ethenomorphinan-7-methanol, hydrochloride [5α, 7α(S)]. Buprenorphine hydrochloride has the molecular formula of C29H41NO4•HCl, the molecular weight of 504.09, and the following structural formula:

INDICATION:

SIMBADOL is indicated for the control of postoperative pain associated with surgical procedures in cats.

DOSAGE AND ADMINISTRATION

The dosage of SIMBADOL is 0.24 mg/kg (0.11 mg/lb) administered subcutaneously once daily, for up to 3 days. Administer the first dose approximately 1 hour prior to surgery.
Do not dispense SIMBADOL for administration at home by the pet owner (see Human Safety).

CONTRAINDICATIONS

SIMBADOL is contraindicated in cats with known hypersensitivity to buprenorphine hydrochloride or any of the components of SIMBADOL, or known intolerance to opioids.

WARNINGS

For subcutaneous (SQ) injectable use in cats.

Human Safety:

Not for use in humans. Keep out of reach of children.

Adult Human User Safety while handling SIMBADOL in the hospital:

Mucous membrane or eye contact during administration:

Direct contact of SIMBADOL with the eyes, oral or other mucous membranes could result in absorption of buprenorphine and the potential for adverse reactions. If accidental eye, oral or other mucous membrane contact is made during administration, flush the area with water and contact a physician.

Skin contact during administration:

If human skin is accidentally exposed to SIMBADOL, wash the exposed areas with soap and water and contact a physician. Accidental exposure could result in absorption of buprenorphine and the potential for adverse reactions.

Drug Abuse, Addiction, and Diversion of Opioids:

Controlled Substance:

SIMBADOL contains buprenorphine, a mu opioid partial agonist and Schedule III controlled substance with an abuse potential similar to other Schedule III opioids. SIMBADOL can be abused and is subject to misuse, abuse, addiction, and criminal diversion. SIMBADOL should be handled appropriately to minimize the risk of diversion, including restriction of access, the use of accounting procedures, and proper disposal methods, as appropriate to the clinical setting and as required by law.

Abuse:

Abuse of SIMBADOL poses a hazard of overdose and death. This risk is increased with concurrent abuse of alcohol and other substances including other opioids and benzodiazepines. Buprenorphine has been diverted for non-medical use into illicit channels of distribution. All people handling opioids require careful monitoring for signs of abuse. Drug abuse is the intentional non-therapeutic use of a prescription drug for its rewarding psychological or physiological effects. Abuse of opioids can occur in the absence of true addiction.

Storage and Discard:

SIMBADOL is a Class III opioid. Store in a locked, substantially constructed cabinet according to DEA and local controlled substance guidelines. Discard broached vials after 28 days. Any unused or expired vials must be destroyed by a DEA registered reverse distributor; for further information, contact your local DEA field office or call Zoetis Inc. at 1-888-963-8471.

Information for physician:

SIMBADOL injectable solution is a mu opioid partial agonist (1.8 mg buprenorphine/ mL). In the case of an emergency, provide the physician with the package insert. Naloxone may not be effective in reversing respiratory depression produced by buprenorphine. The onset of naloxone effect may be delayed by 30 minutes or more. Doxapram hydrochloride has also been used as a respiratory stimulant

PRECAUTIONS

Hyperactivity (opioid excitation) has been observed up to 8 hours after anesthetic recovery (see ADVERSE REACTIONS).
Safety has not been evaluated in moribund cats (i.e., those not expected to live more than 24 hours with or without surgery). Use in such cases should be based on the risk-benefit assessment of the veterinarian.
Use with caution in cats with impaired hepatic function.
The use of SIMBADOL has not been evaluated in breeding, pregnant, or lactating cats, or in cats younger than 4 months of age.

ADVERSE REACTIONS

In two controlled field studies, a total of 450 male and female cats 4 months to 16 years old, weighing between 2.6 – 20.0 lb were included in the field safety analysis. In one study, cats underwent a soft tissue surgical procedure (soft tissue). In the other study, cats underwent onychectomy, onychectomy and castration, or onychectomy and ovariohysterectomy (orthopedic). The following tables (one table for each study) show the number of cats exhibiting each observation.

Adverse Reactions in the Soft Tissue Field Study
Adverse Reactiona | Simbadol (N=109) |  | Control (N=112)
Adverse Reactiona | During Surgeryb | After Surgery | During Surgeryb | After Surgery
Hypotensionc | 39 (35.8%) | 29 (26.6%) | 33 (29.5%) | 24 (21.4%)
Tachycardiad | 26 (23.9%) | 29 (26.6%) | 15 (13.4%) | 20 (17.9%)
Hypothermia (≤98.0ºF) | 30 (27.5%) | 1 (0.9%) | 31 (27.7%) | 0
Hyperthermia (≥103.0ºF) | 0 | 40 (36.7%) | 0 | 19 (17.0%)
Hypertensione | 7 (6.4%) | 20 (18.3%) | 9 (8.0%) | 6 (5.4%)
Anorexia | 0 | 18 (16.5%) | 0 | 15 (13.4%)
Hyperactivity | 0 | 10 (9.2%) | 0 | 4 (3.6%)
Reduced Oxygen Saturation of Hemoglobin (pulse oximetry ≤90%) | 5 (4.6%) | 1 (0.9%) | 8 (7.1%) | 0
Bradycardia (≤90 beats/min) | 2 (1.8%) | 1 (0.9%) | 1 (0.9%) | 0
Tachypnea (≥72 breaths/min) | 0 | 3 (2.8%) | 0 | 2 (1.8%)
Arrhythmia | 1 (0.9%) | 0 | 1 (0.9%) | 0
Hyperesthesia | 0 | 1 (0.9%) | 0 | 0
Blindness | 0 | 1 (0.9%) | 0 | 0
Apnea/Death | 0 | 1 (0.9%) | 0 | 0
a. Cats may have experienced more than one type or occurrence of an adverse reaction. Cats experiencing the same reaction both during and after surgery are presented in both time periods.
b. During surgery is the time from the administration of the anesthetic induction agent until discontinuation of the gas anesthetic.
c. Hypotension is defined as a mean blood pressure of ≤60 mmHg during surgery and ≤90 mmHg after surgery.
d. Tachycardia is defined as a heart rate ≥180 beats per minute during surgery and ≥200 beats per minute after surgery.
e. Hypertension is defined as a mean blood pressure of ≥120 mmHg during surgery and ≥160 mmHg after surgery.

Adverse Reactions in the Orthopedic Field Study
Adverse Reactiona | Simbadol (N=115) |  | Control (N=114)
Adverse Reactiona | During Surgeryb | After Surgery | During Surgeryb | After Surgery
Tachycardiac | 29 (25.2%) | 44 (38.3%) | 15 (13.2%) | 24 (21.1%)
Hypotensiond | 29 (25.2%) | 22 (19.1%) | 27 (23.7%) | 16 (14.0%)
Hyperthermia (≥103.0ºF) | 1 (0.9%) | 51 (44.3%) | 0 | 14 (12.3%)
Anorexia | 0 | 22 (19.1%) | 0 | 20 (17.5%)
Hypertensione | 3 (2.6%) | 20 (17.4%) | 8 (7.0%) | 12 (10.5%)
Hypothermia (≤98.0ºF) | 8 (7.0%) | 0 | 16 (14.0%) | 0
Hyperactivity | 0 | 16 (13.9%) | 0 | 7 (6.1%)
Bradycardia (≤90 beats/min) | 3 (2.6%) | 0 | 3 (2.6%) | 1 (0.9%)
Tachypnea (≥72 beats/min) | 0 | 2 (1.8%) | 1 (0.9%) | 4 (3.5%)
Reduced Oxygen Saturation of Hemoglobin (pulse oximetry ≤90%) | 3 (2.6%) | 0 | 3 (2.6%) | 0
Arrhythmia | 0 | 1 (0.9%) | 1 (0.9%) | 0
Blindness | 0 | 1 (0.9%) | 0 | 1 (0.9%)
Ataxia | 0 | 1 (0.9%) | 0 | 0
Apnea/Death | 1 (0.9%) | 0 | 0 | 0
a. Cats may have experienced more than one type or occurrence of an adverse reaction. Cats experiencing the same reaction both during and after surgery are presented in both time periods.
b. During surgery is the time from the administration of the anesthetic induction agent until discontinuation of the gas anesthetic.
c. Tachycardia is defined as a heart rate ≥180 beats per minute during surgery and ≥200 beats per minute after surgery.
d. Hypotension is defined as a mean blood pressure of ≤60 mmHg during surgery and 90 mmHg after surgery.
e. Hypertension is defined as a mean blood pressure of ≥120 mmHg during surgery and ≥160 mmHg after surgery.

The two cats with apnea in the SIMBADOLTM (buprenorphine injection) group died from the adverse reaction. The cat in the soft tissue study underwent a necropsy and a specific cause of death was not found, although other remarkable findings included metastatic neoplasia affecting multiple systems. The cat in the orthopedic study experienced apnea during endotracheal intubation. The cat was healthy and a specific cause of death was not found.

Two cats in the SIMBADOL group and one cat in the placebo control group were reported with presumptive post-anesthetic cortical blindness. Both cats in the SIMBADOL group received blood pressure intervention during surgery for low blood pressure. All cats regained vision within 7 to 84 days after surgery; however, one cat in the SIMBADOL group continued to have some visual and balance deficits.

One cat in the SIMBADOL group in the soft tissue study was euthanized after completion of the study due to pulmonary complications. The complications were considered likely related to the severity of the cat’s injuries prior to surgery.

Post-Approval Experience (July, 2017):
The following adverse events are based on post-approval adverse drug experience reporting. Not all adverse events are reported to FDA/CVM. It is not always possible to reliably estimate the adverse event frequency or establish a causal relationship to product exposure using these data.

he following adverse events reported for cats are listed in decreasing order of reporting frequency for SIMBADOL: Abnormal behaviors (e.g., hyperactivity, agitation, disorientation, hiding), mydriasis, hyperthermia, anorexia, lethargy, ataxia, and sedation.

CONTACT INFORMATION

To report suspected adverse events, for technical assistance, or to obtain a copy of the Safety Data Sheet (SDS), contact Zoetis Inc. at 1-888-963-8471.
For additional information about adverse drug experience reporting for animal drugs, contact the FDA at 1-888-FDA-VETS or online at http://www.fda.gov/reportanimalae.

CLINICAL PHARMACOLOGY

Buprenorphine is a potent, long-acting analgesic acting at opiate receptors in the central nervous system. Buprenorphine exerts its analgesic effect via high affinity binding to various subclasses of opiate receptors, particularly μ, in the central nervous system.^1 Buprenorphine binds to opiate receptors with high affinity and high receptor avidity, such that its disassociation from the receptor is slow, as demonstrated in in vitro studies. This unique property of buprenorphine could account for its duration of activity.^1

Following subcutaneous injection in cats, there is considerable inter-cat variability in plasma concentration and pharmacokinetic parameters.^2 Formulated as an immediate release product, buprenorphine is quickly absorbed after subcutaneous injection. Pharmacological effects (e.g., mydriasis) may occur within minutes after injection. Buprenorphine plasma concentrations following subcutaneous injection did not appear to correlate to pharmacodynamics measurements (change in the thermal threshold data). In studies with SIMBADOL analgesic effects of buprenorphine appeared about one hour after injection with a 24 to 28 hour duration of action. Combined pharmacokinetic and pharmacodynamic studies have demonstrated a marked time delay between plasma concentrations and the onset and offset of the analgesic effect which is due to the slow equilibration between drug concentrations in the biophase and the slow association and dissociation of drug binding to the receptor. ^2,3

Buprenorphine is metabolized in the liver. The major route of excretion of buprenorphine is in the feces. Buprenorphine undergoes oxidative metabolism by N-dealkylation to form norbuprenorphine (an active metabolite) via CYP3A4. Buprenorphine and norbuprenorphine subsequently form inactive glucuronide conjugates in the intestinal wall and the liver and its metabolites are excreted via the bile into the gastro-intestinal tract.^4 The elimination half-life in cats is reported to be similar to that associated with humans and slower than that observed in dogs.^5 It is also noted that because the cat is devoid of uridine diphosphate glucuronosyltransferase enzymes, conjugated metabolites may be absent.^5

EFFECTIVENESS

The effectiveness of SIMBADOL was demonstrated in two randomized, masked, placebo-controlled, multi-site field studies involving client-owned cats of various breeds. In one study (soft tissue), 221 cats underwent a soft tissue surgical procedure. In the other study (orthopedic), 229 cats underwent an onychectomy alone or in combination with castration or ovariohysterectomy. Cats received either a subcutaneous injection of 0.24 mg/kg of SIMBADOL or physiologic saline approximately 60 minutes prior to surgery at the same time as pre-anesthetic medication. SIMBADOL or physiologic saline was given once daily for two additional treatments 24 and 48 hours after the initial treatment. A descriptive, interactive pain assessment system was used by the trained assessor over the 72 hour post-operative period to determine pain control. Treatment success was defined as a cat that made it through the entire 72 hour period without rescue analgesia. In the soft tissue field study, a statistically significant difference in the proportion of treatment successes in the SIMBADOL treatment group (66/93 or 71.0%) compared to the placebo control group (45/102 or 44.1%) was observed. Twenty-seven out of 93 (29.0%) SIMBADOL cases and 57 out of 102 (55.9%) placebo cases were treatment failures. In the orthopedic field study, a statistically significant difference in the proportion of treatment successes in the SIMBADOL treatment group (64/105 or 61.0%) compared to the placebo control group (33/102 or 32.4%) was observed. Forty-one out of 105 (39.0%) SIMBADOL cases and 69 out of 102 (67.6%) placebo cases were treatment failures. For both studies, the majority of the treatment failures required rescue within 4 hours after anesthetic recovery.

Combining both studies (450 cats), sedation was observed in 68 cats in the buprenorphine group and 62 cats in the placebo control group for up to 4 hours after anesthetic recovery. In both studies, during surgery, mean respiratory rates and mean blood pressures were lower in the buprenorphine group compared to the placebo control group. There were a higher number of cats and a higher number of incidences of pain on injection in the buprenorphine group (20 cats, 28 incidences) compared to the placebo control group (8 cats, 10 incidences).

The results of two field studies demonstrate that SIMBADOL is effective and has an acceptable safety margin for the control of postoperative pain in cats.

ANIMAL SAFETY

Nine-Day Target Animal Safety Study: In a 9 day safety study, 4 month old healthy cats (4/sex/group) were administered SIMBADOL subcutaneously at 0X (saline), 1X (0.24 mg/kg), 3X (0.72 mg/kg), or 5X (1.2 mg/kg) once daily. All 32 cats survived to study termination.

Buprenorphine-related clinical observations included difficulty in handling, lower incidence of urination, abnormal oral dryness, dilated pupils, and decreased pupillary light reflex. The incidence of temperatures ≥103°F was higher in the buprenorphine-treated groups compared to the control group. The highest temperature observed in the buprenorphine-treated group was 103.8°F in a 5X cat.

One 1X cat and one 3X cat experienced an episode of hyperactivity, difficulty in handling, slight disorientation, agitation, dilated pupils (which were responsive to light), and respiratory sinus arrhythmia. One 1X cat (one episode) and one 3X cat (three episodes) were reported with nystagmus. One 1X and one 3X cat were reported with decreased blink response (one episode). Three cats in the 5X group lost body weight (79 g or less) during the study which correlated with decreased food consumption. All other cats gained weight during the study.

The incidence of “moderate responses” (minor vocalization or wincing and quick resolution) and “severe responses” (tried to bite or scratch or had marked vocalization or persistent attention to the injection site) to injection was higher in the buprenorphine-treated groups compared to the control group.

Respiratory rate, heart rate, and blood pressure were similar between all groups, including the control group.

Buprenorphine-related clinical pathology findings included an increase in creatine kinase values in the 3X and 5X groups and correlated with subcutaneous inflammation at the injection sites.

Histologic lesions included minimal to moderate subacute inflammation at the injection sites, which correlated with the administration of buprenorphine compared to the control group. The incidence of inflammation was similar between buprenorphine-treated groups; however, more sites with mild and moderate inflammation were observed in the 5X group compared to the 1X and 3X groups where more sites with minimal inflammation were observed. Mineralization at an injection site was seen in one 1X and one 3X cat. Chronic inflammation in the heart (valve or myocardium) was seen in two 5X cats. Subacute liver inflammation was seen in one control cat, two 1X cats, three 3X cats, and three 5X cats. Lymphoid hyperplasia of the mediastinal lymph node was seen in one 1X cat, and acute inflammation was seen in the mediastinal lymph node of one 3X cat. Lymphoid hyperplasia of the Peyer’s Patches was seen in two 1X cats and one 5X cat. Lymphoid hyperplasia, lymphocytic infiltrate, or subacute inflammation of the stomach was seen in four 1X cats, four 3X cats, and three 5X cats. Subacute inflammation or lymphocytic infiltrate of the thyroid glands was seen in two 1X cats, one 3X cat, and four 5X cats.

Arterial Blood Pressure Study in Cats: Healthy 8.5 to 29.1 month old cats (4/sex/group) were subcutaneously administered SIMBADOL at 0.24 mg/kg (1X) or meloxicam (control), 1 hour prior to anesthetic induction for a 1 hour exploratory laparotomy. Arterial blood pressure was monitored following anesthetic induction and through laparotomy, with indirect blood pressure monitoring prior to anesthesia and for 8 hours following anesthetic recovery. All 16 animals were clinically healthy for the duration of the study. There were no differences between treatment groups in mean blood pressure during the study.

During surgery and postoperatively, heart rate was higher for the buprenorphine group. During surgery, the incidence of heart rates ≥180 beats/minute was higher in the buprenorphine-treated group compared to the control group. Post-operatively, the incidence of heart rates ≥200 beats/minute was higher in the buprenorphine-treated group compared to the control group. During surgery, respiration rate was lower for the buprenorphine group. Post-operatively, body temperature was higher for the buprenorphine group. Four cats in the buprenorphine group had temperatures ≥103°F post-operatively compared to none in the control group. The highest temperature observed in the buprenorphine group was 104.3°F. Electrocardiograms were qualitatively normal in all cats. During surgery, one cat in the buprenorphine group had hemoglobin saturation less than 90% (88% at one time point).

STORAGE INFORMATION

Store at temperatures up to 25°C (77°F). Protect from light and excessive heat (above 40°C or 104°F). Use within 56 days of first puncture.

HOW SUPPLIED

SIMBADOL (buprenorphine injection) is supplied in a carton containing one 10 mL amber glass vial. Each multidose vial contains 1.8 mg/mL of buprenorphine.
Approved by FDA under NADA # 141-434

REFERENCES

1. Heel RC, Brogden RN, Speight TM, et al. Buprenorphine: a review of its pharmacological
properties and therapeutic efficacy. Drugs 1979;17:81-110.
2. Steagall PV, Pelligand L, Giordano T, et al. Pharmacokinetic and pharmacodynamic modelling of
intravenous, intramuscular and subcutaneous buprenorphine in conscious cats. Vet Anaesth Analg
2013;40:83-95.
3. Robertson SA, Lascelles BD, Taylor PM, et al. PK-PD modeling of buprenorphine in cats:
intravenous and oral transmucosal administration. J Vet Pharmacol Ther 2005;28:453-460.
4. Brewster D, Humphrey MJ, McLeavy MA. Biliary excretion, metabolism and enterohepatic circulation
of buprenorphine. Xenobiotica 1981;11:189-196.
5. Court MH. Feline drug metabolism and disposition: pharmacokinetic evidence for species
differences and molecular mechanisms. Vet Clin Small Anim 2013;43: 1039-1054.

Distributed by:
Zoetis Inc.
Kalamazoo, MI 49007
Revised: September 2022
50270803